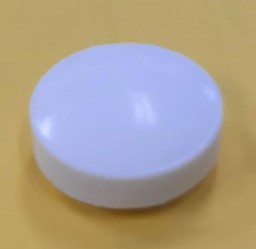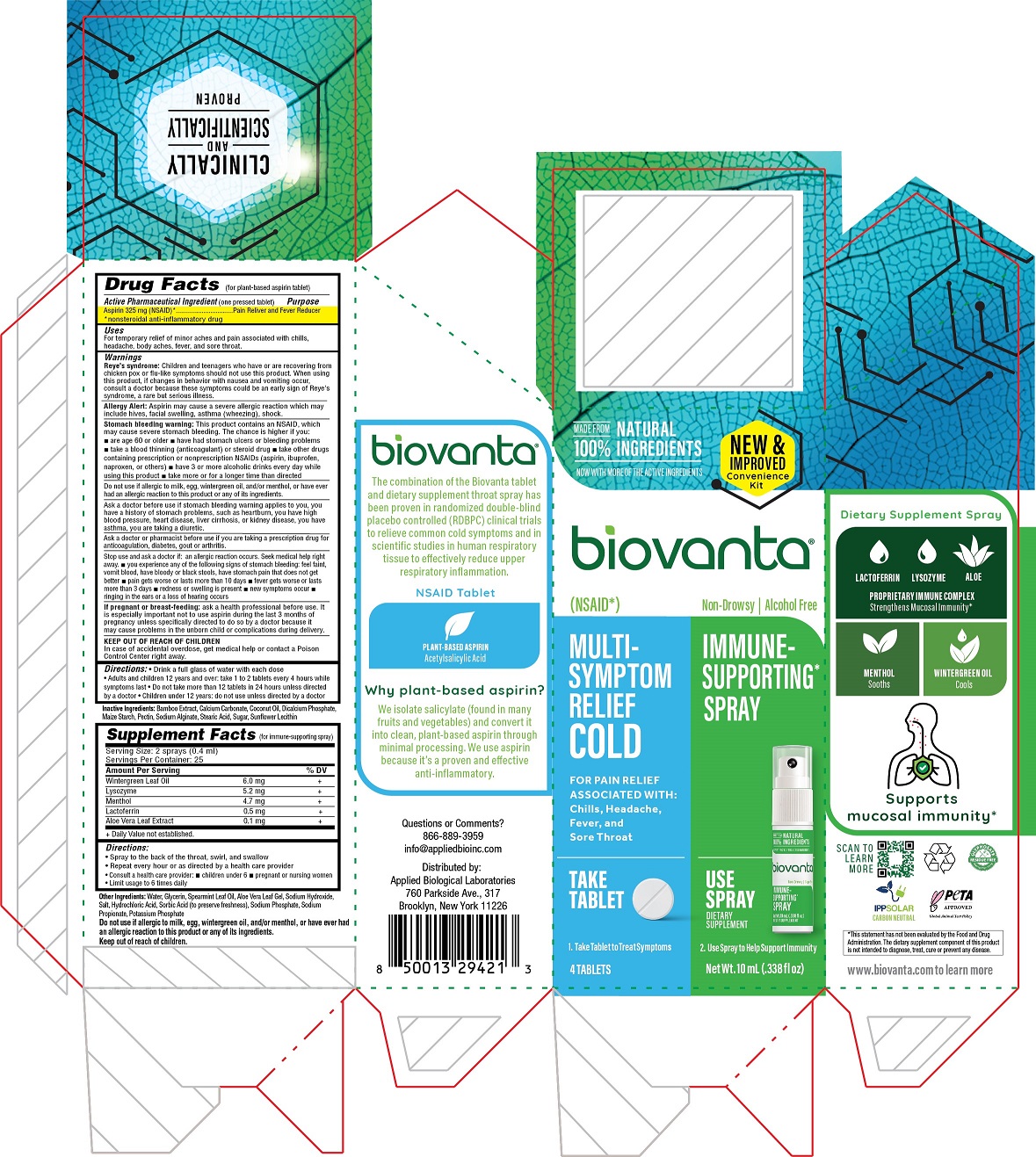 DRUG LABEL: Natural Aspirin plus Immune Supporting Dietary Supplement
NDC: 73678-103 | Form: KIT | Route: ORAL
Manufacturer: Applied Biological Laboratories Inc.
Category: otc | Type: HUMAN OTC DRUG LABEL
Date: 20230428

ACTIVE INGREDIENTS: ASPIRIN 325 mg/1 1
INACTIVE INGREDIENTS: CALCIUM PHOSPHATE, DIBASIC, ANHYDROUS; STARCH, CORN; PECTIN; SUCROSE; STEARIC ACID; LECITHIN, SUNFLOWER; CALCIUM CARBONATE; COCONUT OIL; BAMBUSA VULGARIS TOP; SODIUM ALGINATE

Biovanta New & Improved Convenience Kit: Natural Aspirin Tablet + Immune Supporting Dietary Supplement Throat Spray

Active ingredient

Aspirin 325 mg (NSAID)*

*nonsteroidal anti-inflammatory drug

Purpose

Pain reliever and fever reducer

Uses

For temporary relief of minor aches and pain associated with chills, headache, body aches, fever, and sore throat.

Warnings

Reye's syndrome: Children and teenagers who have or are recovering from chicken pox or flu-like symptoms should not use this product. When using this product, if changes in behavior with nausea and vomiting occur, consult a doctor because these symptoms could be an early sign of Reye's syndrome, a rare but serious illness.

Allergy Alert: Aspirin may cause a severe allergic reaction which may include hives, facial swelling, asthma (wheezing), shock.

Stomach bleeding warning: This product contains an NSAID, which may cause severe stomach bleeding. The chance is higher if you: • are age 60 or older • have had stomach ulcers or bleeding problems • take a blood thinning (anticoagulant) or steroid drug • take other drugs containing prescription or nonprescription NSAIDs (aspirin, ibuprofen, naproxen, or others) • have 3 or more alcoholic drinks every day while using this product • take more or for a longer time than directed.

Do not use if allergic to milk, egg, wintergreen oil, and/or menthol, or have ever had an allergic reaction to this product or any of its ingredients.

Ask a doctor before use if stomach bleeding warning applies to you, you have a history of stomach problems, such as heartburn, you have high blood pressure, heart disease, liver cirrhosis, or kidney disease, you have asthma, you are taking a diuretic.

Ask a doctor or pharmacist before use if you are taking a prescription drug for anticoagulation, diabetes, gout or arthritis.

Stop use and ask a doctor if: an allergic reaction occurs. Seek medical help right away. • you experience any of the following signs of stomach bleeding: feel faint, vomit blood, have bloody or black stools, have stomach pain that does not get better • pain gets worse or lasts more than 10 days • fever gets worse or lasts more than 3 days • redness or swelling is present • new symptoms occur • ringing in the ears or a loss or hearing occurs

PREGNANCY OR BREAST FEEDING

If Pregnant or Breast-feeding: Ask a health professional before use. It is especially important not to use aspirin during the last 3 months of pregnancy unless specifically directed to do so by a doctor because it may cause problems in the unborn child or complications during delivery.

KEEP OUT OF REACH OF CHILDREN

In case of accidental overdose, get medical help or contact a Poison Control Center right away.

Directions

- Drink a full glass of water with each dose
- Adults and children 12 years and over: Take 1 to 2 tablets every 4 hours while symptoms last
- Do not take more than 12 tablets in 24 hours unless directed by a doctor
- Children under 12 years: do not use unless directed by a doctor

Inactive ingredients

Bamboo extract, calcium carbonate, coconut oil, dicalcium phosphate, maize starch, pectin, sodium alginate, stearic acid, sugar, sunflower lecithin

biovanta®

(NSAID*) Non-Drowsy | Sugar Free

MULTI-SYMPTOM RELIEF COLD

FOR PAIN RELIEF ASSOCIATED WITH: Chills, Headache, Fever, and Sore Throat

TAKE TABLET

1. Take Tablet to Treat Symptoms

4 TABLETS

Questions or Comments?

866-889-3959

info@appliedbioinc.com

Distributed by:

Applied Biological Laboratories

760 Parkside Ave., 317

Brooklyn, New York 11226

IMMUNE-SUPPORTING* SPRAY

USE SPRAY

DIETARY SUPPLEMENT

2. Use Spray to Help Support Immunity

Net Wt. 10 mL (.338 fl oz)